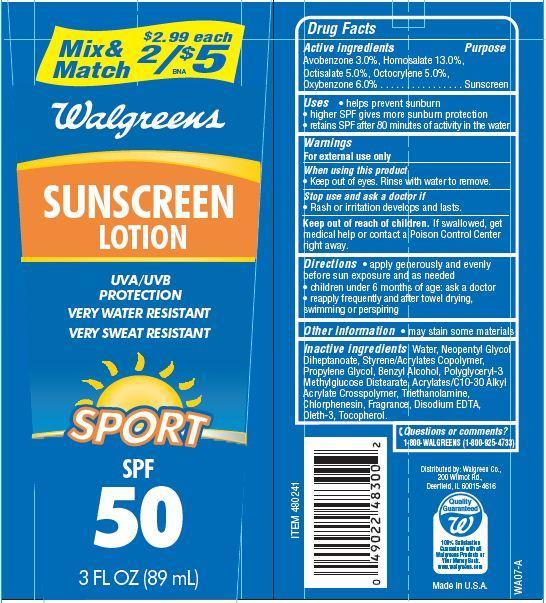 DRUG LABEL: Walgreens Sunscreen Sport
NDC: 0363-4011 | Form: LOTION
Manufacturer: WALGREEN CO.
Category: otc | Type: HUMAN OTC DRUG LABEL
Date: 20121204

ACTIVE INGREDIENTS: AVOBENZONE 3 g/100 g; HOMOSALATE 13 g/100 g; OCTISALATE 5 g/100 g; OCTOCRYLENE 5 g/100 g; OXYBENZONE 6 g/100 g
INACTIVE INGREDIENTS: WATER; NEOPENTYL GLYCOL DIHEPTANOATE; PROPYLENE GLYCOL; TROLAMINE; CHLORPHENESIN; BENZYL ALCOHOL; OLETH-3; TOCOPHEROL; EDETATE DISODIUM

Drug Facts

Active Ingredients

Avobenzone 3.0 %

Homosalate 13.0%

Octisalate 5.0%

Octocrylene 5.0%

Oxybenzone 6.0%

Purpose

Sunscreen

Uses

- helps prevent sunburn
- higher SPF gives more sunburn protection
- retains SPF after 80 minutes of activity in the water

Warnings

For external use only

When using this product

- keep out of eyes. Rinse with water to remove.

stop use and ask a doctor if

- Rash or irritation develops and lasts

Keep out of reach of children.

If swallowed get medical help or contact a Poison Control Center right away.

Directions

- apply generously and evenly before sun exposure and as needed
- children under 6 months of age:ask a doctor
- reapply frequently and after towel drying, swimming or perspiring.

Inactive Ingredients

Water, Neopentyl Glycol Diheptanoate, Styrene/Acrylates Copolymer, Propylene Glycol, Polyglyceryl-3 Methylglucose Distearate, Benzyl Alcohol, Acrylates/C10-30 Alkyl Acrylate Crosspolymer, Triethanolamine, Disodium EDTA, Oleth-3, Tocopherol, Chlorphenesin, Fragrance.

Other Information

- may stain some materials

Questions or comments?

1-800-WALGREENS (1-800-925-4733)

Principal Display Panel

Mix and Match $2.99 each
2/$5
Walgreens
SUNSCREEN
LOTION
UVA.UVB
PROTECTION
VERY WATER RESISTANT
VERY SWEAT RESISTANT
SPORT
SPF
50
3 FL OZ (89 mL)